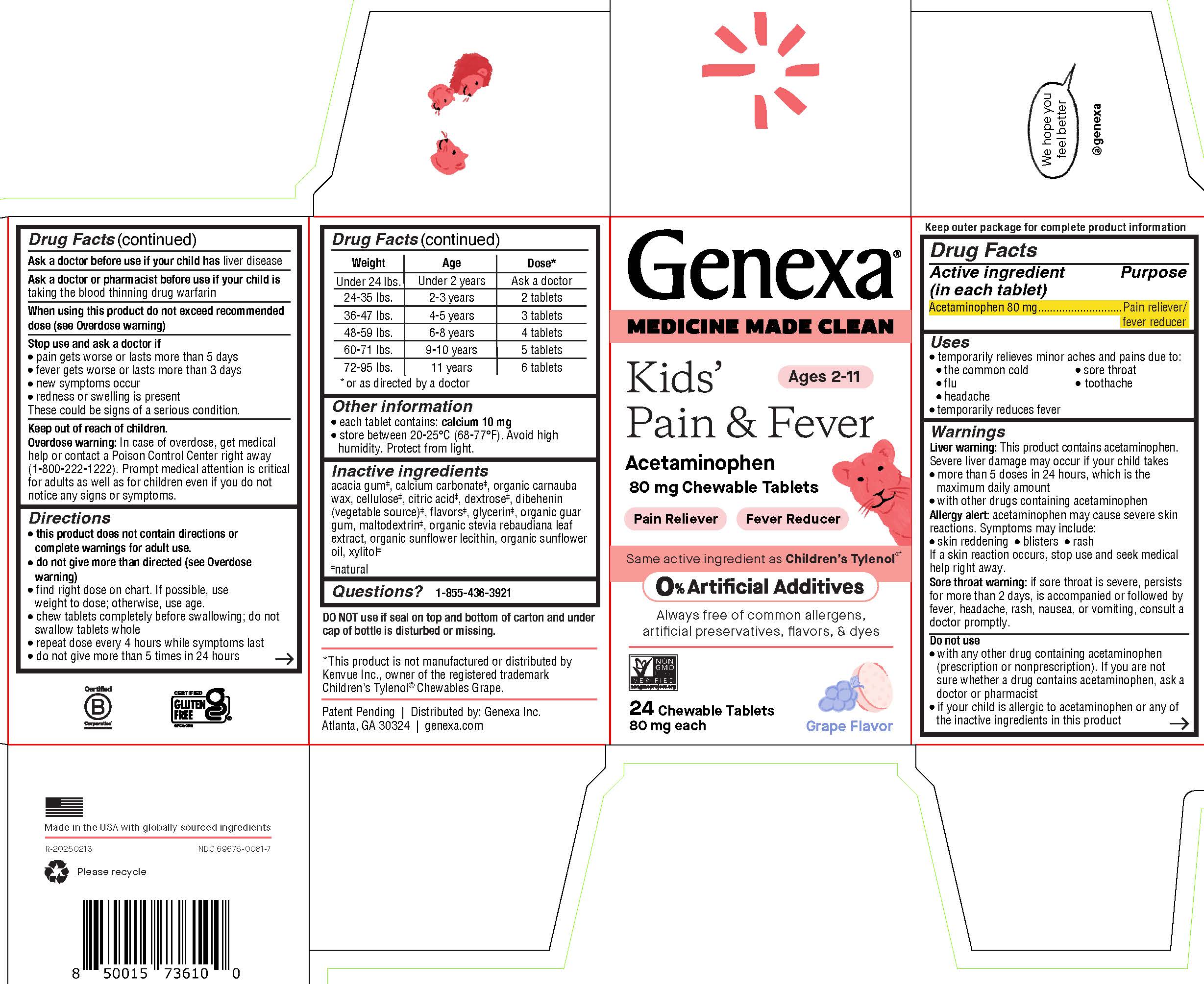 DRUG LABEL: Genexa Kids Pain and Fever
NDC: 69676-0081 | Form: TABLET, CHEWABLE
Manufacturer: Genexa, Inc.
Category: otc | Type: HUMAN OTC DRUG LABEL
Date: 20250624

ACTIVE INGREDIENTS: ACETAMINOPHEN 80 mg/1 1
INACTIVE INGREDIENTS: SUNFLOWER OIL; MALTODEXTRIN; STEVIA REBAUDIUNA LEAF; DEXTROSE; CARNAUBA WAX; GUAR GUM; CALCIUM CARBONATE; GLYCERIN; XYLITOL; ACACIA; GLYCERYL DIBEHENATE; LECITHIN, SUNFLOWER; CITRIC ACID MONOHYDRATE

Kids Pain and Fever Chewable Tablets

Drug Facts

Active ingredient (in each tablet)

Acetaminophen 80 mg

Purpose

Pain reliever/fever reducer

Uses

• temporarily relieves minor aches and pains due to:
• the common cold
• flu
• headache
• sore throat
• toothache
• temporarily reduces fever

Warnings

Liver warning: This product contains acetaminophen. Severe liver damage may occur if your child takes

- more than 5 doses in 24 hours, which is the maximum daily amount
- with other drugs containing acetaminophen

Allergy alert: acetaminophen may cause severe skin reactions. Symptoms may include:

- skin reddening
- blisters
- rash

If a skin reaction occurs, stop use and seek medical help right away.

Sore throat warning: if sore throat is severe, persists for more than 2 days, is accompanied or followed by fever, headache, rash, nausea, or vomiting, consult a doctor promptly.

Do not use

- with any other drug containing acetaminophen (prescription or nonprescription). If you are not sure whether a drug contains acetaminophen, ask a doctor or pharmacist
- if your child is allergic to acetaminophen or any of the inactive ingredients in this product

Ask a doctor before use if your child has liver disease

Ask a doctor or pharmacist before use if your child is taking the blood thinning drug warfarin

When using this product do not exceed recommended dose (see Overdose warning)

Stop use and ask a doctor if

- pain gets worse or lasts more than 5 days
- fever gets worse or lasts more than 3 days
- new symptoms occur
- redness or swelling is present

These could be signs of a serious condition

Keep out of reach of children.

OVERDOSAGE

Overdose warning: In case of overdose, get medical help or contact a Poison Control Center right away (1-800-222-1222). Prompt medical attention is critical for adults as well as for children even if you do not notice any signs or symptoms.

Directions

- this product does not contain directions or complete warnings for adult use.
- do not give more than directed (see Overdose warning)
- find right dose on chart below. If possible, use weight to dose; otherwise, use age.
- chew tablets completely before swallowing; do not swallow tablets whole
- repeat dose every 4 hours while symptoms last
- do not give more than 5 times in 24 hours

Weight | Age | Dose*
Under 24 lbs. | Under 2 years | Ask a doctor
24-35 lbs. | 2-3 years | 2 tablets
36-47 lbs. | 4-5 years | 3 tablets
48-59 lbs. | 6-8 years | 4 tablets
60-71 lbs. | 9-10 years | 5 tablets
72-95 lbs. | 11 years | 6 tablets

*or as directed by a doctor

Other information

- each tablet contains: calcium 10 mg
- store between 20-25oC (68-77oF). Avoid high humidity. Protect from light.

Inactive ingredients

acacia gum‡, calcium carbonate‡, organic carnauba wax, cellulose‡, citric acid‡, dextrose‡, dibehenin (vegetable source)‡, flavors‡, glycerin‡, organic guar gum, maltodextrin‡, organic stevia rebaudiana leaf extract, organic sunflower lecithin, organic sunflower oil, xylitol‡

‡ natural

Questions? 1-855-436-3921

DO NOT use if seal on top and bottom of carton and under cap of bottle is disturbed or missing.

*This product is not manufactured or distributed by Kenvue Inc., owner of the registered trademark Children's Tylenol® Chewables Grape.

Patent Pending | Distributed by: Genexa Inc.

Atlanta, GA 30324 | genexa.com

Made in the USA with globally sourced ingredients

NDC 69676-0081-7

PACKAGE LABEL

Genexa®

MEDICINE MADE CLEAN

Ages 2-11

Kids' Pain & Fever

Acetaminophen

80 mg Chewable Tablets

Pain Reliever

Fever Reducer

Same active ingredient as Children's Tylenol®*

0% Artificial Additives

Always free of common allergens, artificial preservatives, flavors, & dyes

24 Chewable Tablets

80 mg each

Grape Flavor